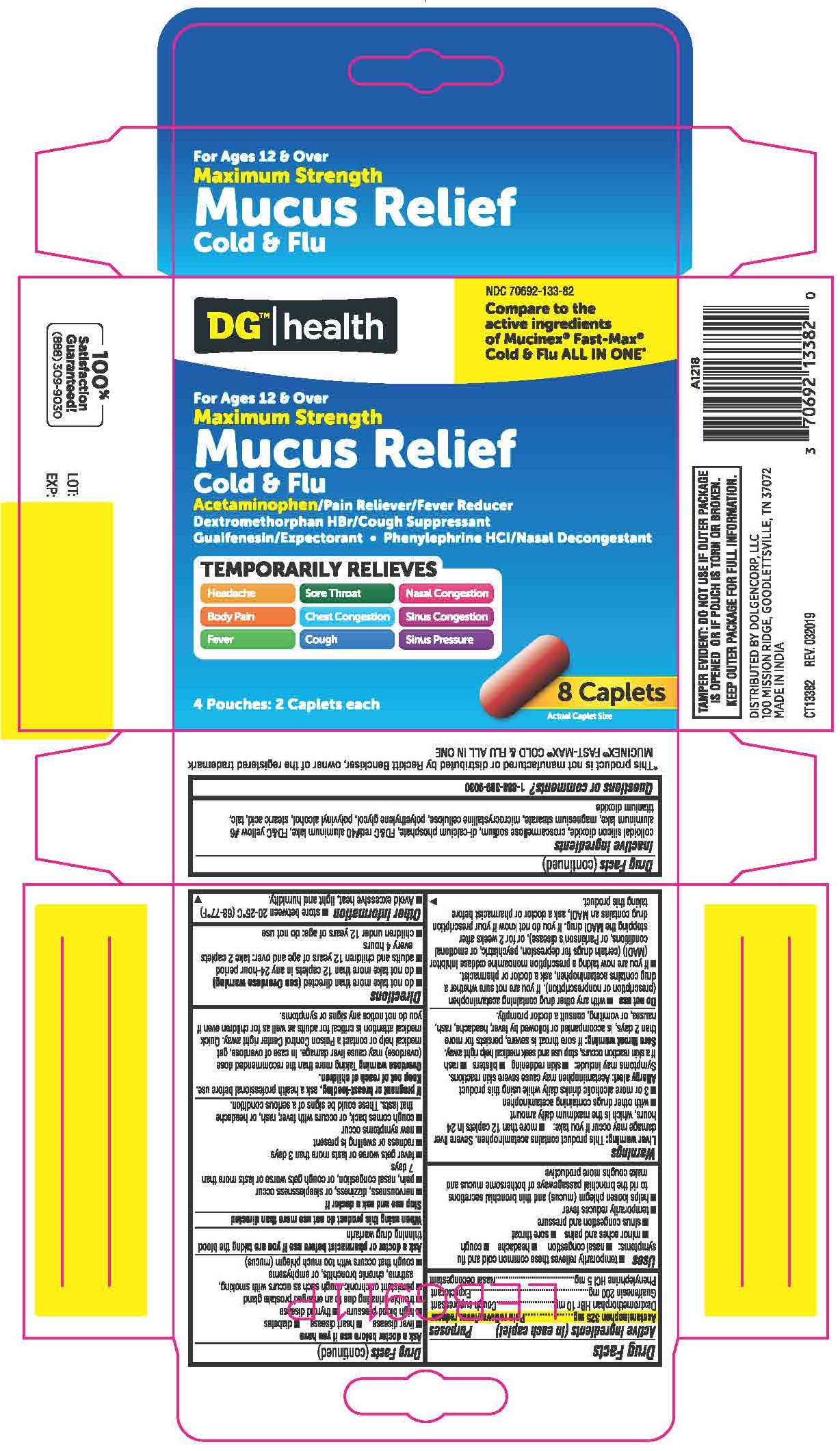 DRUG LABEL: Acetaminophen Dextromethorphan HBr Guaifenesin Phenylephrine HCl
NDC: 70692-133 | Form: TABLET, COATED
Manufacturer: Strive Pharmaceuticals Inc.
Category: otc | Type: HUMAN OTC DRUG LABEL
Date: 20201109

ACTIVE INGREDIENTS: PHENYLEPHRINE HYDROCHLORIDE 5 mg/1 1; GUAIFENESIN 200 mg/1 1; ACETAMINOPHEN 325 mg/1 1; DEXTROMETHORPHAN HYDROBROMIDE 10 mg/1 1
INACTIVE INGREDIENTS: CROSCARMELLOSE SODIUM; TALC; TITANIUM DIOXIDE; MAGNESIUM STEARATE; SILICON DIOXIDE; CALCIUM PHOSPHATE; MICROCRYSTALLINE CELLULOSE; POLYETHYLENE GLYCOL 400; POLYVINYL ALCOHOL, UNSPECIFIED; STEARIC ACID; FD&C RED NO. 40; FD&C YELLOW NO. 6

DGH MS Mucus Relief Cold & Flu
Acetaminophen 325mg, Dextromethorphan HBr 10mg, Guaifenesin 200mg, Phenylephrine HCl 5mg

ACTIVE INGREDIENT

Acetaminophen 325mg

Dextromethorphan HBr 10mg

Guaifenesin 200mg

Phenylephrine HCl 5mg

PURPOSE

Pain reliever/fever reducer

Cough suppressant

Expectorant

Nasal decongestant

INACTIVE INGREDIENT

colloidal silicon dioxide, croscarmellose sodium, di-calcium phosphate, FD&C red #40 aluminum lake, FD&C yellow #6 aluminum lake, magnesium stearate, microcrystalline cellulose, polyethylene glycol, polyvinyl alcohol, stearic acid, talc, titanium dioxide

DOSAGE AND ADMINISTRATION

- do not take more than directed (see overdose warning)
- do not take more than 12 caplets in any 24 hour period
- adults and children 12 years of age and over: take 2 caplets every 4 hours
- children under 12 years of age: do not use

INDICATIONS AND USAGE

- temporarily relieves these common cold and flu symptoms: *headache *cough *minor aches and pains *sore throat *sinus congestion and pressure
- tempoararily reduces fever
- helps loosen phlegm (mucus) and thin bronchial secretions to rid the bronchial passageways of bothersome mucus and make coughs more productive

WARNINGS

Liver warning: This product contains acetaminophen. Severe liver damage may occur if you take:

- more than 12 capltes in 24 hours, which is the maximum daily amount
- with other drugs containing acetaminophen
- 3 or more alcoholic drink daily while using this product

Allergy alert: Acetaminophen may cause severe skin reactions. Symptoms may include:

- skin reddening
- blisters
- rash

If skin raction occurs, stop use and seek medical help right away.

Sore throat warning: If sore throat is severe, persists for more than 2 days, is accompanied or followed by fever, headache, rash, nausea, or vomiting, consult a doctor promptly.

Do not use

- with any other drug containing acetaminophen (prescription or nonprescription). If you are not sure whether a drug contains acetaminophen, ask a doctor or pharmacist.
- if you are now taking a prescription monoamine oxidase inhibitor (MAOI) (certain drugs for depression, psychiatric, or emotional conditions, or Parkinson's disease), or for 2 weeks after stopping the MAOI drug. If you do not know if your prescription drug contains an MAOI, ask a doctor or pharmacist before taking this product.

Ask a doctor before use if you have

- liver disease
- heart disease
- diabetes
- high blood pressure
- thyroid disease
- trouble urinating due to an enlarged prostate gland
- persistent or chronic cough such as occurs with smoking, asthma, chronic bronchitis, or emphysema
- cough that occurs with too much phlegm (mucus)

Ask a doctor or pharmacist before use if you are taking the blood thinning drug warfarin

When using this product do not use more than directed

Stop use and ask a doctor if

- nervousness, dizziness, or sleeplessness occur
- pain, nasal congestion, or cough gets worse or lasts more than 7 days
- fever gets worse or lasts more than 3 days
- redness or swelling is present
- new symptoms occur
- cough comes back, or occurs with fever, rash, or headache that lasts. These could be signs of a serious condition.

If pregnant or breast-feeding, ask a health professional before use.

Keep out of reach of children.

Overdose Warning: Taking more than the recommended dose (overdose) may cause liver damage. In case of overdose, get medical help or contact a Poison Control Center right away. Quick medical attention is critical for adult as well as for children even if you do not notice any signs or symptoms.

Keep out of reach of children.

OVERDOSAGE

Overdose Warning: Taking more than the recommended dose (overdose) may cause liver damage. In case of overdose, get medical help or contact a Poison Control Center right away. Quick medical attention is critical for adult as well as for children even if you do not notice any signs or symptoms.

OTHER SAFETY INFORMATION

- store between 20-25°C (68-77ºF).
- avoid excessive heat, light and humidity.